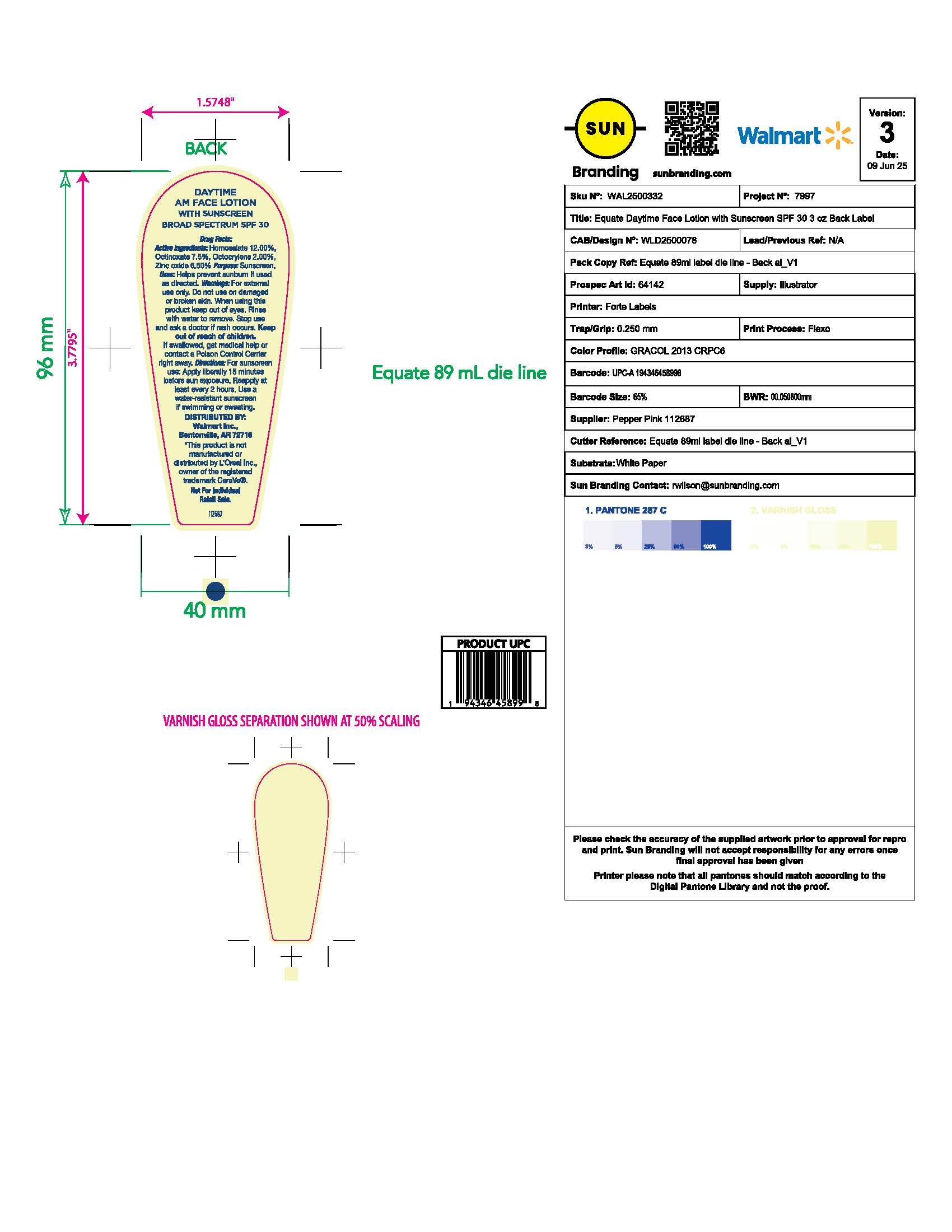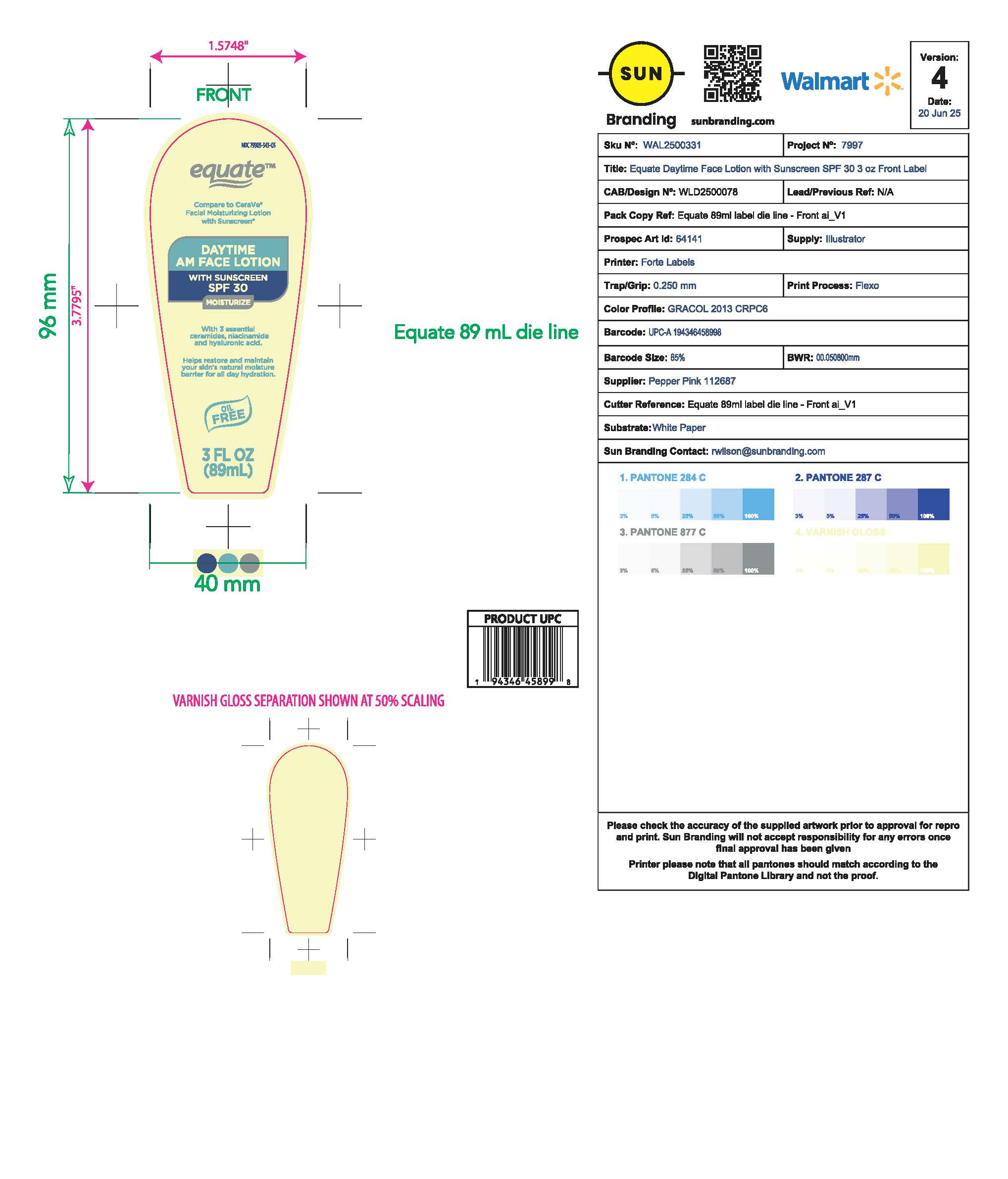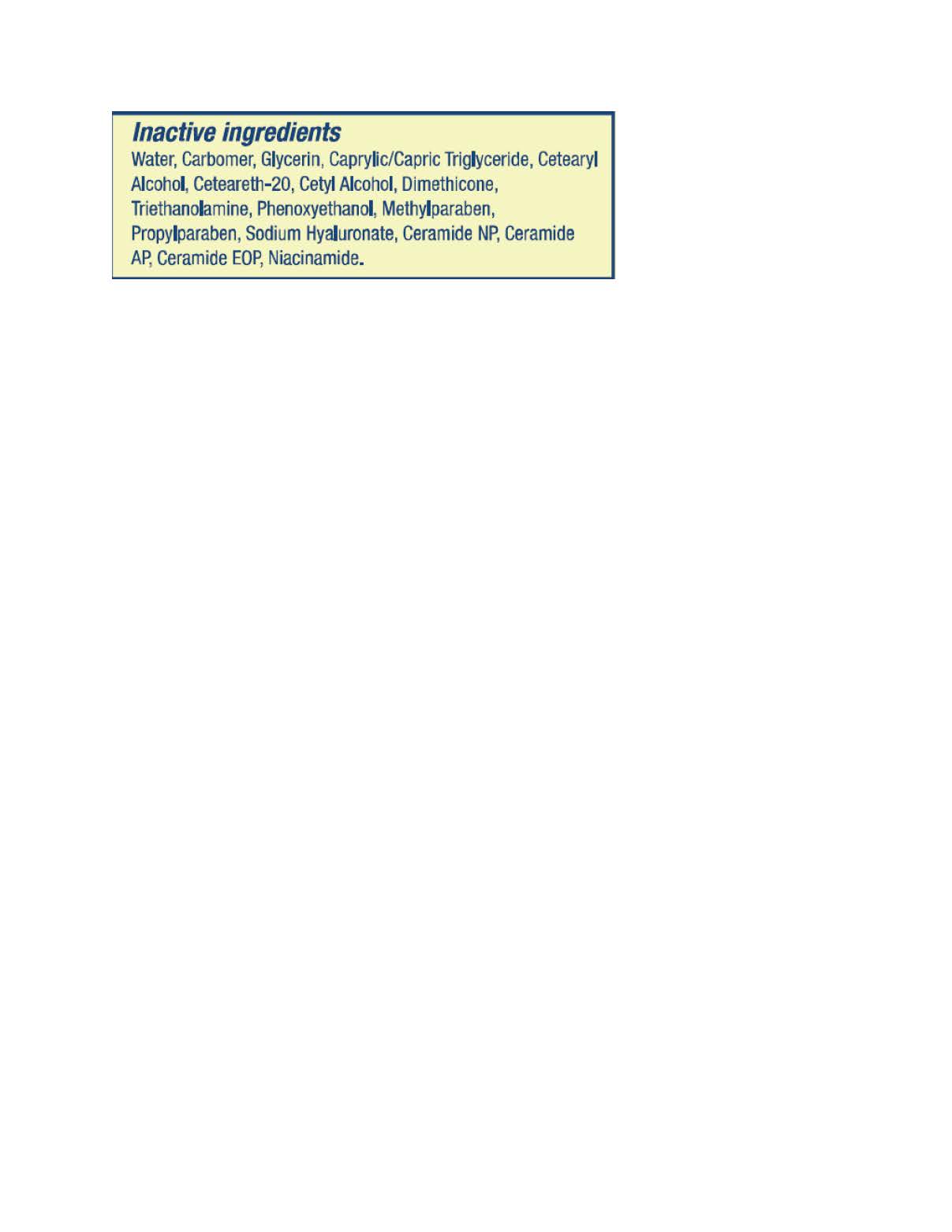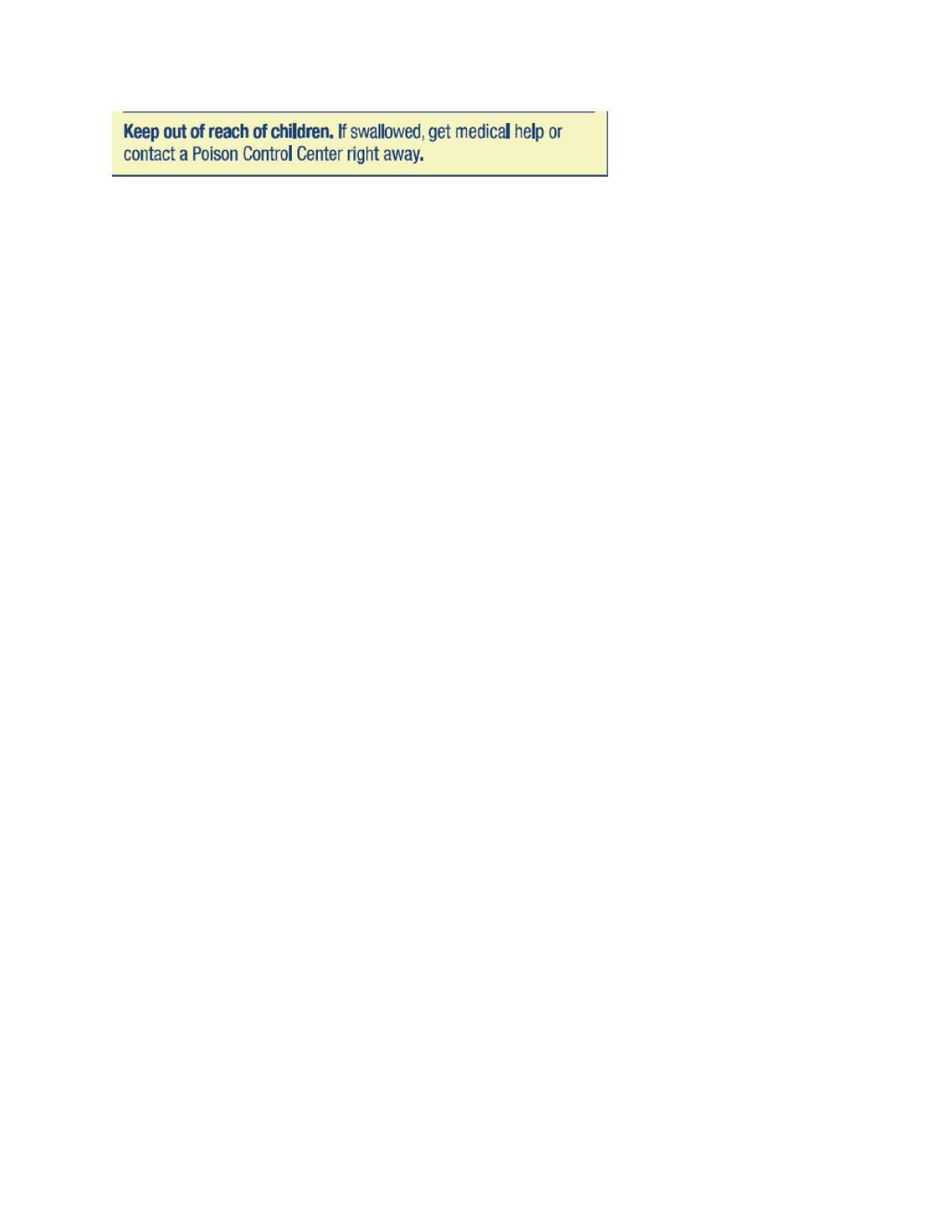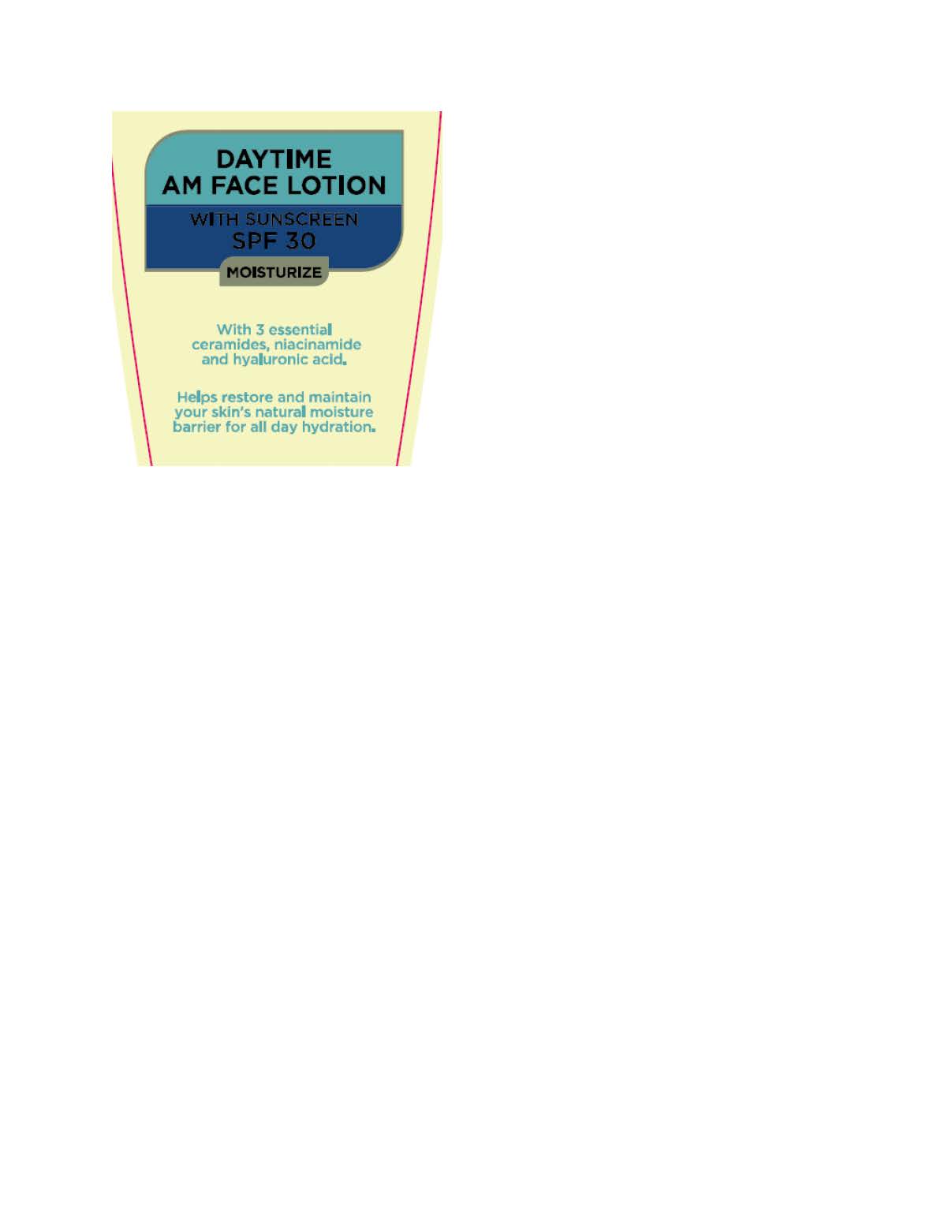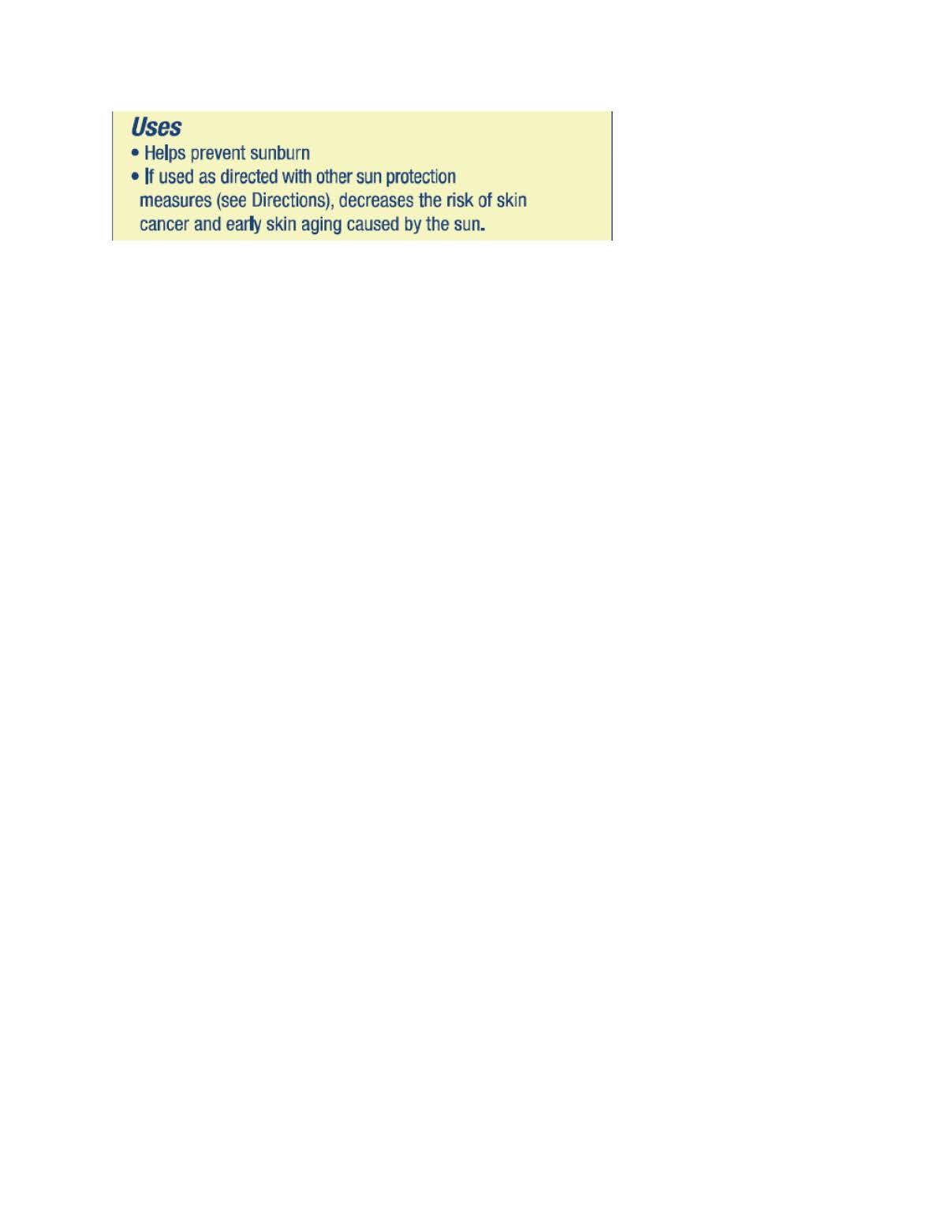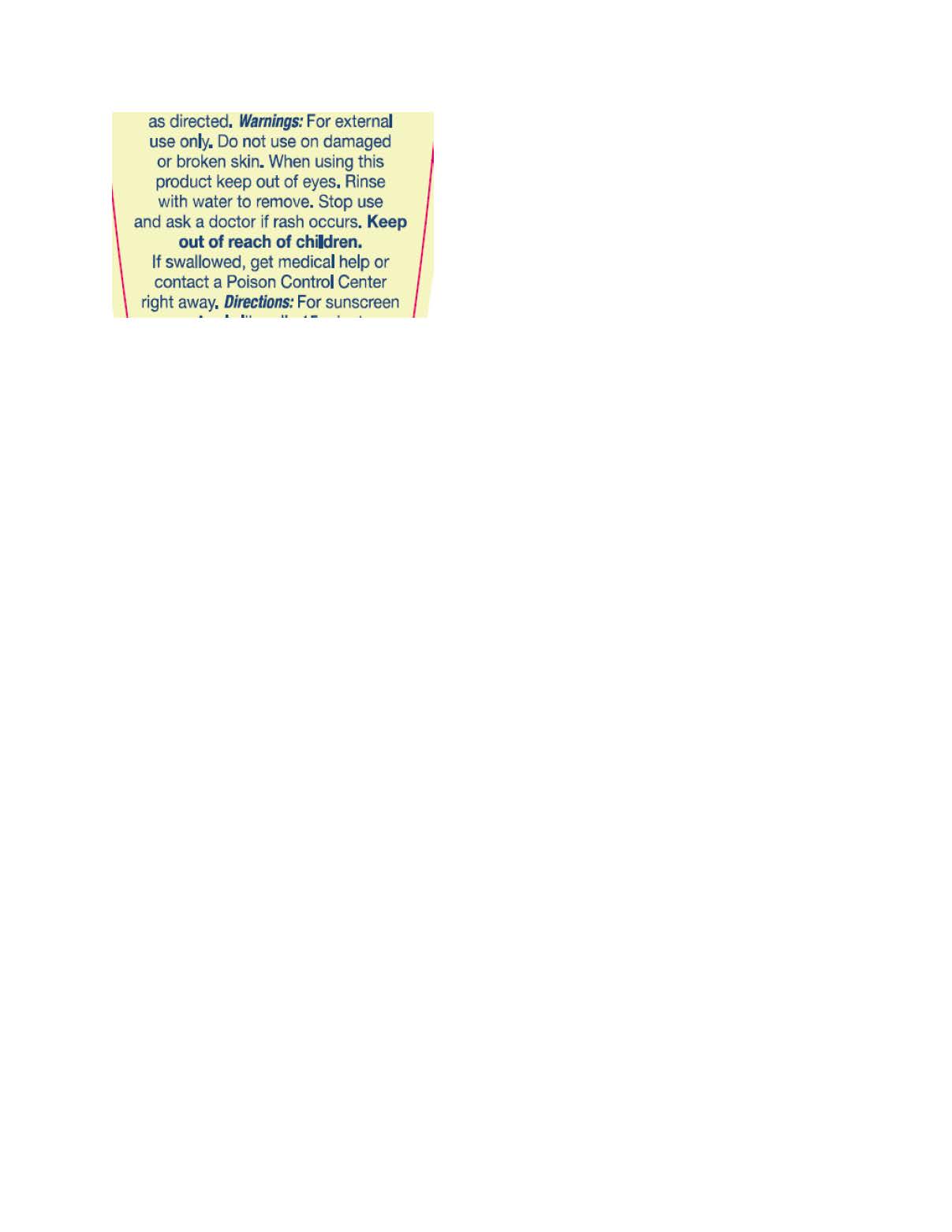 DRUG LABEL: EquateDaytimeFaceLotion
NDC: 79903-343 | Form: LOTION
Manufacturer: Walmart Inc.
Category: otc | Type: HUMAN OTC DRUG LABEL
Date: 20250918

ACTIVE INGREDIENTS: ZINC OXIDE 0.65 kg/100 kg
INACTIVE INGREDIENTS: GLYCERIN 0.2 kg/100 kg

Equate Daytime AM Face Lotion with Sunscreen SPF 30

PACKAGE LABEL

Active Ingredients

Purpose

Warnings

Keep out reach of children

Directions